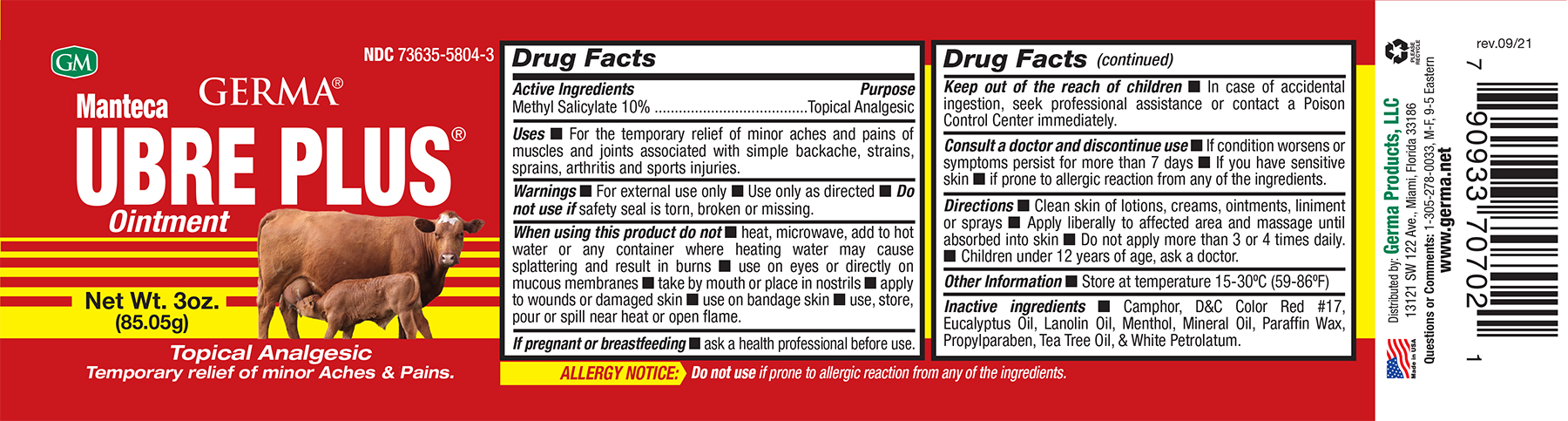 DRUG LABEL: Germa Manteca Ubre Plus (RED)
NDC: 73635-5804 | Form: OINTMENT
Manufacturer: Germa Products, LLC
Category: otc | Type: HUMAN OTC DRUG LABEL
Date: 20251010

ACTIVE INGREDIENTS: METHYL SALICYLATE 100 mg/1 mL
INACTIVE INGREDIENTS: WHITE PETROLATUM; D&C RED NO. 17; TEA TREE OIL; MENTHOL; PROPYLPARABEN; LANOLIN OIL; EUCALYPTUS OIL; CAMPHOR (SYNTHETIC); MINERAL OIL; PARAFFIN

Manteca Ubre Plus (RED)

Active Ingredient

Methyl Salicylate 10%

Uses

For the temporary relief of minor aches and pains of muscles and joints associated with simple backache, strains, sprains, arthritis and sports injuries.

When using this product do not • heat, microwave, add to hot water or any container where heating water may cause splattering and result in burns • use on eyes or directly on mucous membranes • take by mouth or place in nostrils • apply to wounds or damaged skin • use on bandage skin • use, store, pour or spill near heat or open flame.

Purpose

Topical Analgesic

Warnings

For external use only ■ Use only as directed

Do not use • on children • with a heating pad • with a tight bandage • on eyes, mucous membranes, wound or irritated skin • over extensive areas of the body.

Warnings

KEEP OUT OF THE REACH OF CHILDREN

In case of accidental ingestion, seek professional assistance or contact a Poison Control Center immediately.

PREGNANCY OR BREAST FEEDING

If pregnant or breast-feeding, ask a health professional before use.

ASK DOCTOR

Consult a doctor and discontinue use • If condition worsens or symptoms persist for more than 7 days • If you have sensitive skin • if prone to allergic reaction from any of the ingredients.

Other Information

Store at controlled room temperature 15-30ºC (59-86ºF)

Directions

Clean skin of lotions, creams, ointments, liniment or sprays • Apply liberally to affected area and massage until absorbed into skin • Do not apply more than 3 or 4 times daily. • Children under 12 years of age, ask a doctor.

Inactive Ingredients

Camphor, D&C Color Red #17, Eucalyptus Oil, Lanolin Oil, Menthol, Mineral Oil, Paraffin Wax, Propylparaben, Tea Tree Oil, White Petrolatum.

Principal Display Panel

Manteca Ubre Plus Red